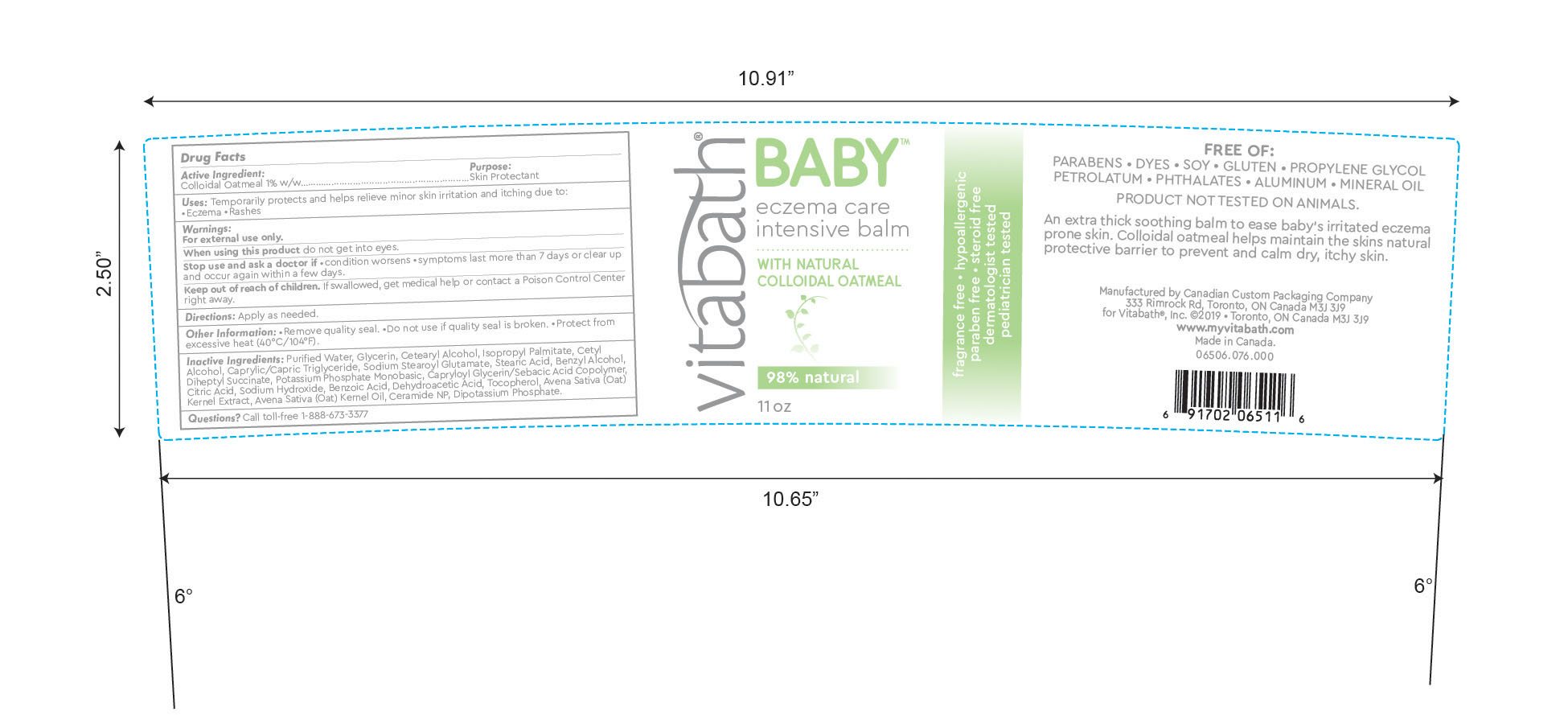 DRUG LABEL: Vitabath Baby Eczema Care Intensive Balm
NDC: 73172-003 | Form: CREAM
Manufacturer: Vitabath Inc.
Category: otc | Type: HUMAN OTC DRUG LABEL
Date: 20190613

ACTIVE INGREDIENTS: OATMEAL 1 g/100 g
INACTIVE INGREDIENTS: CITRIC ACID MONOHYDRATE; SODIUM HYDROXIDE; DEHYDROACETIC ACID; TOCOPHEROL; OAT KERNEL OIL; BENZOIC ACID; OAT; CERAMIDE NP; POTASSIUM PHOSPHATE, MONOBASIC; CAPRYLOYL GLYCERIN/SEBACIC ACID COPOLYMER (2000 MPA.S); DIBASIC POTASSIUM PHOSPHATE; DIHEPTYL SUCCINATE; WATER; GLYCERIN; CETOSTEARYL ALCOHOL; ISOPROPYL PALMITATE; CETYL ALCOHOL; MEDIUM-CHAIN TRIGLYCERIDES; SODIUM STEAROYL GLUTAMATE; STEARIC ACID; BENZYL ALCOHOL

Vitabath Baby Eczema Care Intensive Balm

Active Ingredients

Colloidal Oatmeal 1% w/w

Purpose

Skin protectant

Uses

Temporarily protects and helps relieve minor skin irritation and itching due to:
•Eczema • Rashes

Warnings

For external use only.

When using this product do not get into eyes.

Stop use and ask a doctor if • condition worsens • symptoms last more than 7 days or clear up
and occur again within a few days.

Keep out of reach of children. If swallowed, get medical help or contact a Poison Control Center
right away..

Directions

Directions: Apply as needed.

OTHER INFORMATION

Other Information: •Remove quality seal. •Do not use if quality seal is broken. •Protect from
excessive heat (40°C/104°F).

Inactive Ingredients

Purified Water
Glycerin
Cetearyl Alcohol
Isopropyl Palmitate
Cetyl Alcohol
Caprylic/Capric Triglyceride
Sodium Stearoyl Glutamate
Stearic Acid
Benzyl Alcohol
Diheptyl Succinate
Potassium Phosphate Monobasic
Capryloyl Glycerin/Sebacic Acid Copolymer
Citric Acid
Sodium Hydroxide
Benzoic Acid
Dehydroacetic Acid
Tocopherol
Avena Sativa (Oat) Kernel Extract
Avena Sativa (Oat) Kernel Oil
Ceramide NP
Dipotassium Phosphate

Questions? Call toll-free 1-888-673-3377